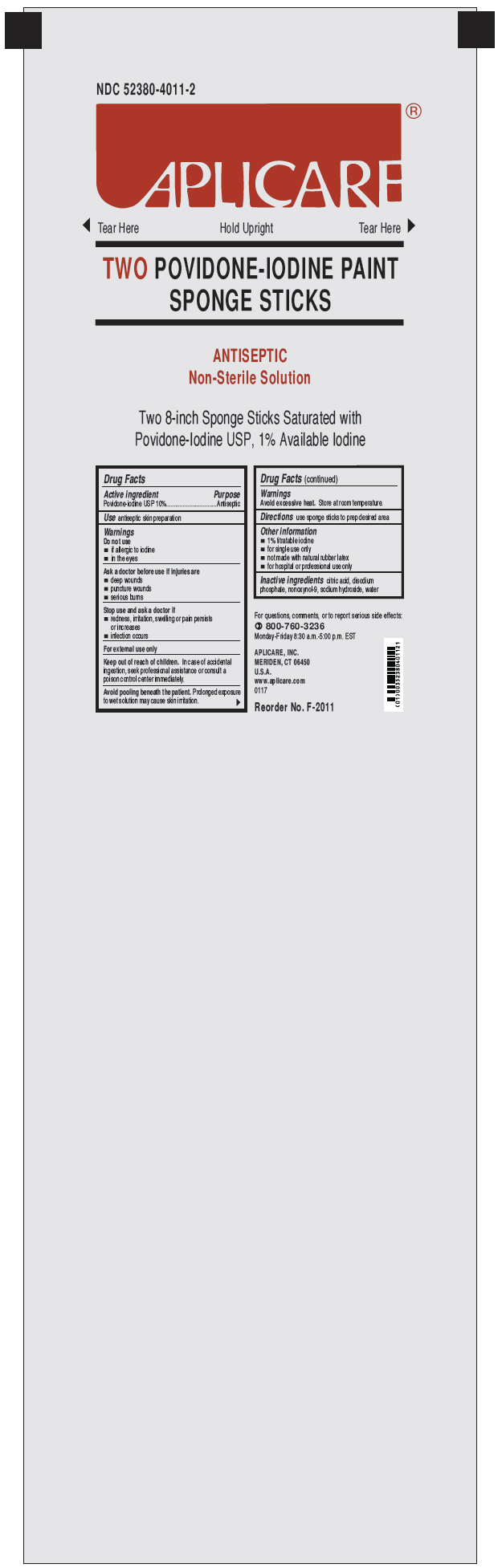 DRUG LABEL: Aplicare Povidone-Iodine Paint
NDC: 52380-4011 | Form: SOLUTION
Manufacturer: Aplicare, Inc.
Category: otc | Type: HUMAN OTC DRUG LABEL
Date: 20170601

ACTIVE INGREDIENTS: POVIDONE-IODINE 10 mg/1 mL
INACTIVE INGREDIENTS: CITRIC ACID MONOHYDRATE; SODIUM PHOSPHATE, DIBASIC; SODIUM HYDROXIDE; NONOXYNOL-9; WATER

Aplicare Povidone-Iodine Paint

Drug Facts

Active ingredient

Povidone-iodine USP 10%

Purpose

Antiseptic

Use

antiseptic skin preparation

Warnings

Do not use

- if allergic to iodine
- in the eyes

Ask a doctor before use if injuries are

- deep wounds
- puncture wounds
- serious burns

Stop use and ask a doctor if

- redness, irritation, swelling or pain persists or increases
- infection occurs

For external use only

Keep out of reach of children. In case of accidental ingestion, seek professional assistance or consult a poison control center immediately.

Avoid pooling beneath the patient. Prolonged exposure to wet solution may cause skin irritation.

STORAGE AND HANDLING

Avoid excessive heat. Store at room temperature.

Directions

use sponge sticks to prep desired area

Other information

- 1% titratable iodine
- for single use only
- not made with natural rubber latex
- for hospital or professional use only

Inactive ingredients

citric acid, disodium phosphate, nonoxynol-9, sodium hydroxide, water

QUESTIONS

For questions, comments, or to report serious side effects:

800-760-3236

Monday-Friday 8:30 a.m.-5:00 p.m. EST

PRINCIPAL DISPLAY PANEL - 2 Sponge Sticks Packet

NDC 52380-4011-2

APLICARE

◀ Tear Here Hold Upright Tear Here ▶

TWO POVIDONE-IODINE PAINT
SPONGE STICKS

ANTISEPTIC
Non-Sterile Solution

Two 8-inch Sponge Sticks Saturated with
Povidone-Iodine USP, 1% Available Iodine

Reorder No. F-2011